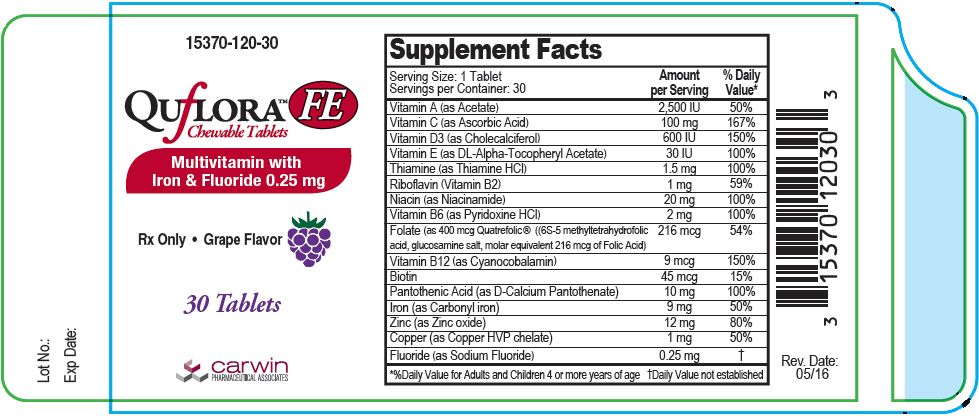 DRUG LABEL: Quflora FE
NDC: 15370-120 | Form: TABLET, CHEWABLE
Manufacturer: CarWin Pharmaceutical Associates, LLC
Category: other | Type: DIETARY SUPPLEMENT
Date: 20160715

ACTIVE INGREDIENTS: VITAMIN A ACETATE 2500 [iU]/1 1; ASCORBIC ACID 100 mg/1 1; CHOLECALCIFEROL 600 [iU]/1 1; .ALPHA.-TOCOPHEROL, DL- 30 [iU]/1 1; THIAMINE HYDROCHLORIDE 1.5 mg/1 1; RIBOFLAVIN 1 mg/1 1; NIACINAMIDE 20 mg/1 1; PYRIDOXINE HYDROCHLORIDE 2 mg/1 1; LEVOMEFOLATE GLUCOSAMINE 216 ug/1 1; CYANOCOBALAMIN 9 ug/1 1; BIOTIN 45 ug/1 1; CALCIUM PANTOTHENATE 10 mg/1 1; IRON PENTACARBONYL 9 mg/1 1; ZINC OXIDE 12 mg/1 1; COPPER 1 mg/1 1; SODIUM FLUORIDE 0.25 mg/1 1
INACTIVE INGREDIENTS: CITRIC ACID MONOHYDRATE; SILICON DIOXIDE; MAGNESIUM STEARATE; CELLULOSE, MICROCRYSTALLINE; GRAPE; SORBITOL; STEARIC ACID; SUCRALOSE; XYLITOL

QUfLORA™ FE
Chewable Tablets

STATEMENT OF IDENTITY

Supplement Facts
Serving Size: 1 Tablet Servings per Container: 30
 | Amount per Serving | % Daily Value [%Daily Value for Adults and Children 4 or more years of age]
Vitamin A (as Acetate) | 2500 IU | 50%
Vitamin C (as Ascorbic Acid) | 100 mg | 167%
Vitamin D3 (as Cholecalciferol) | 600 IU | 150%
Vitamin E (as DL-Alpha Tocopheryl Acetate) | 30 IU | 100%
Thiamine (as Thiamine HCl) | 1.5 mg | 100%
Riboflavin (Vitamin B2) | 1 mg | 59%
Niacin (as Niacinamide) | 20 mg | 100%
Vitamin B6 (as Pyridoxine HCl) | 2 mg | 100%
Folate (as 400 mcg Quatrefolic® ((6S-5 methyltetrahydrofolic acid, glucosamine salt, molar equivalent 216 mcg of Folic Acid) | 216 mcg | 54%
Vitamin B12 (as Cyanocobalamin) | 9 mcg | 150%
Biotin | 45 mcg | 15%
Pantothenic Acid (as D-Calcium Pantothenate) | 10 mg | 100%
Iron (as Carbonyl iron) | 9 mg | 50%
Zinc (as Zinc oxide) | 12 mg | 80%
Copper (as Copper HVP chelate) | 1 mg | 50%
Fluoride (as Sodium Fluoride) | 0.25 mg | [Daily Value not established]

Other Ingredients: Citric acid, fumed silica, magnesium stearate, microcrystalline cellulose, natural grape flavor, silicon dioxide, sorbitol, stearic acid, sucralose and xylitol.

INDICATIONS AND USAGE

Quflora™ FE Chewable Tablets Multivitamin with Iron and Fluoride 0.25mg is a prescription dietary fluoride supplement providing essential vitamins and minerals.

CONTRAINDICATIONS

Quflora™ FE Chewable Tablets Multivitamin with Iron and Fluoride 0.25 mg should not be used by patients with a known history of hypersensitivity to any of the listed ingredients.

PRECAUTIONS

General

The suggested dose should not be exceeded, since dental fluorosis may result from continued ingestion of large amounts of fluoride. Do not eat or drink dairy products within one hour of fluoride administration. Incompatibility of fluoride with dairy foods has been reported due to formation of calcium fluoride which is poorly absorbed. Your healthcare practitioner can prescribe the correct dosage.

Folic Acid

Folic Acid alone is improper therapy in the treatment of pernicious anemia and other megaloblastic anemias where vitamin B12 is deficient. Folic acid in doses above 0.1 mg daily may obscure pernicious anemia in that hematologic remission can occur while neurological manifestations progress.

ADVERSE REACTIONS

Allergic rash and other idiosyncrasies have been rarely reported. Call your doctor for medical advice about side effects. You may report side effects or obtain product information by calling Carwin Pharmaceutical Associates, LLC at 1-844-700-5011.

WARNINGS

WARNING: Accidental overdose of iron-containing products is a leading cause of fatal poisoning in children under 6. KEEP THIS PRODUCT OUT OF REACH OF CHILDREN. In case of accidental overdose, call a doctor or poison control center immediately.

DOSAGE AND ADMINISTRATION

One tablet daily or as prescribed by your healthcare practitioner. This product should be chewed and is not recommended for children under age 4.

DESCRIPTION

Quflora™ FE Chewable Tablets is a gray with yellowish tint, round tablet imprinted "120".

HOW SUPPLIED

Quflora™ FE Chewable Tablets are available in child-resistant bottles of 30 (Product Code: 15370-120-30).

Rx Only

STORAGE

Store at controlled room temperature 20° C to 25° C (68° F to 77° F), excursions permitted between 15° C and 30° C (59° F and 86° F). Protect from light, moisture and excessive heat.

THIS PRODUCT CONTAINS IRON.

SAFE HANDLING WARNING

KEEP THIS PRODUCT OUT OF REACH OF CHILDREN.

TAMPER EVIDENT: Do not use if seal is broken or missing.

Quatrefolic® is a registered trademark of Gnosis, SpA. Covered by one or more claims of U.S. Patent # 7,947,662 CAS# 1181972-37-1

HEALTH CLAIM

Manufactured for:
Carwin Pharmaceutical Associates, LLC
Hazlet, NJ 07730
www.carwinpharma.com

Made in Canada

Rev. 5/16

PRINCIPAL DISPLAY PANEL - 30 Tablet Bottle Label

15370-120-30

QUfLORA™ FE
Chewable Tablets

Multivitamin with
Iron & Fluoride 0.25 mg

Rx Only • Grape Flavor

30 Tablets

carwin
PHARMACEUTICAL ASSOCIATES